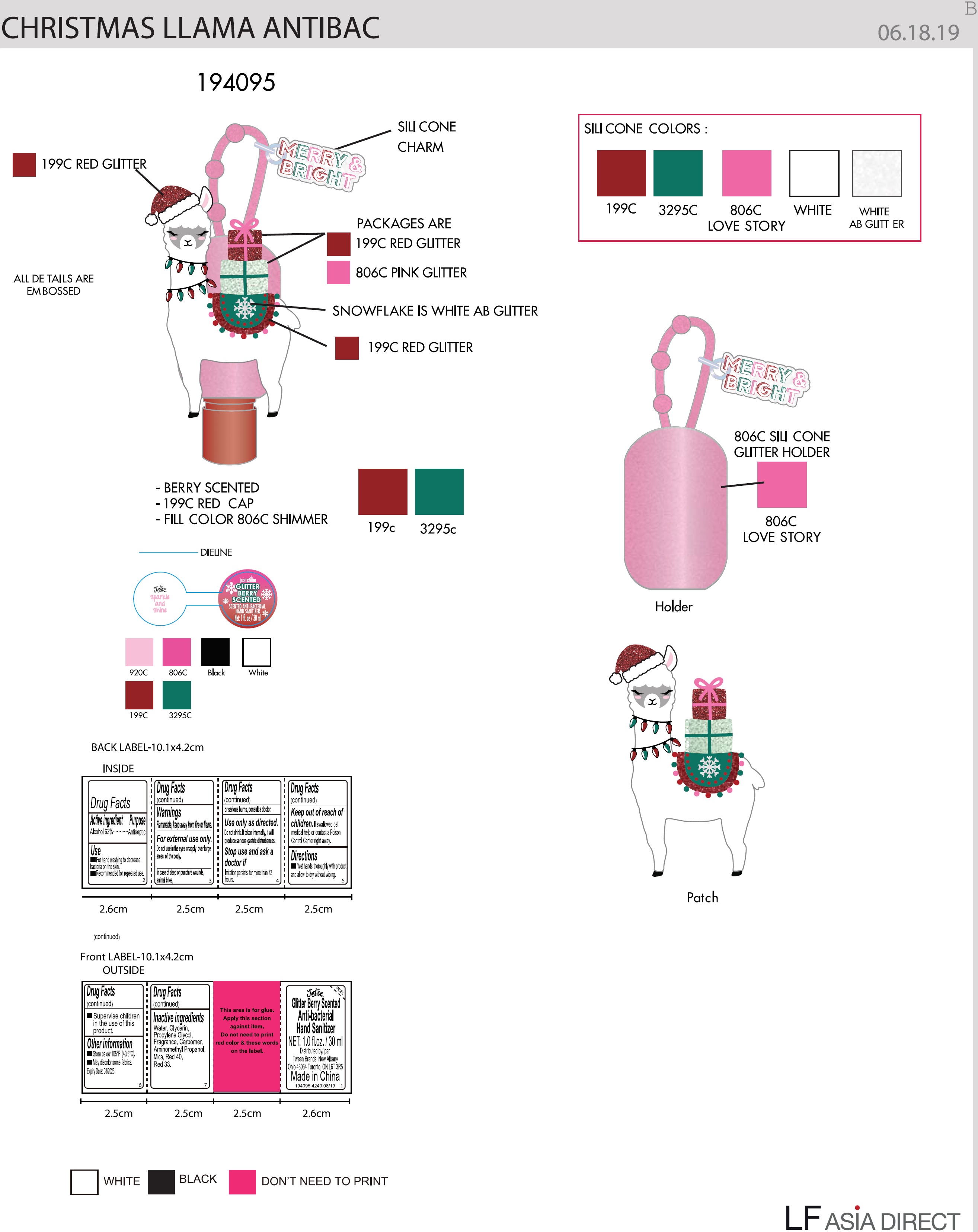 DRUG LABEL: 
                  Justice Glitter Berry Scented Anti-bacterial Hand Sanitizer
                
                  

NDC: 60637-119 | Form: GEL
Manufacturer: Tween Brands, Inc.
Category: otc | Type: HUMAN OTC DRUG LABEL
Date: 20231026

ACTIVE INGREDIENTS: ALCOHOL 620 mg/1 mL
INACTIVE INGREDIENTS: WATER; GLYCERIN; PROPYLENE GLYCOL; CARBOXYPOLYMETHYLENE; AMINOMETHYLPROPANOL; MICA; FD&C RED NO. 40; D&C RED NO. 33

Justice Glitter Berry Scented Anti-bacterial Hand Sanitizer - Llama

Active ingredient

Alcohol 62%

Purpose

Antiseptic

Use

- For hand washing to decrease bacteria on the skin.
- Recommended for repeated use.

Warnings

Flammable, keep away from fire or flame.

For external use only.

Do not use

in the eyes or apply over large areas of the body.

In case of deep or puncture wounds, animal bites, or serious burns, consult a doctor.

Use only as directed. Do not drink. If taken internally, it will produce serious gastric disturbances.

Stop use and ask a doctor if

irritation persists for more than 72 hours.

Keep out of reach of children.

If swallowed get medical help or contact a Poison Control Center right away.

Directions

- Wet hands thoroughly with product and allow to dry without wiping.
- Supervise children in the use of this product.

Other information

- Store below 105°F (40.5°C).
- May discolor some fabrics.

Expiry Date:08/2023

Inactive ingredients

Water, Glycerin, Propylene Glycol, Fragrance, Carbomer, Aminomethyl Propanol, Mica, Red 40, Red 33.